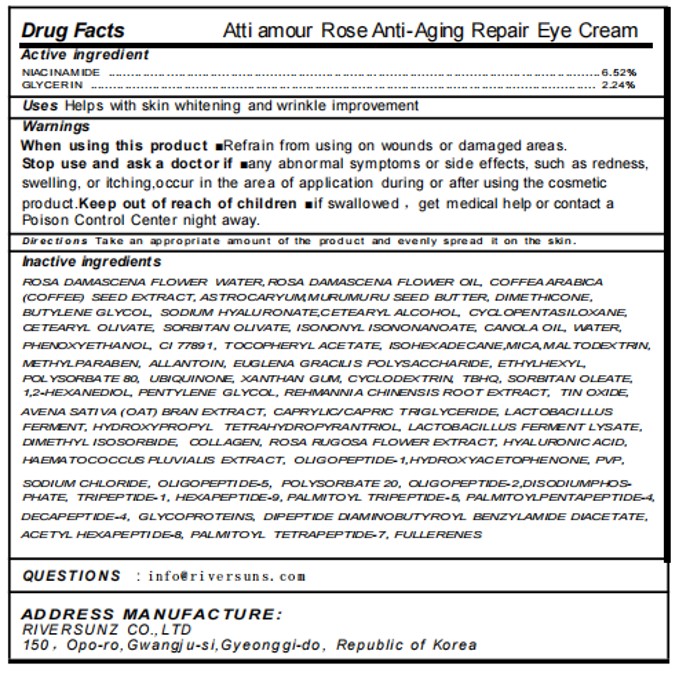 DRUG LABEL: Atti amour Rose Anti-Aging Repair Eye Cream
NDC: 84601-003 | Form: CREAM
Manufacturer: RIVER SUNZ co.,Ltd
Category: otc | Type: HUMAN OTC DRUG LABEL
Date: 20251106

ACTIVE INGREDIENTS: NIACINAMIDE 6.52 g/100 g; GLYCERIN 2.24 g/100 g
INACTIVE INGREDIENTS: CYCLODEXTRINS; DIMETHYL ISOSORBIDE; ARABICA COFFEE BEAN; CETEARYL OLIVATE; CETOSTEARYL ALCOHOL; CYCLOMETHICONE 5; MICA; HYDROXYPROPYL TETRAHYDROPYRANTRIOL; SODIUM PHOSPHATE, DIBASIC, ANHYDROUS; ALPHA-TOCOPHEROL ACETATE; DIPEPTIDE DIAMINOBUTYROYL BENZYLAMIDE DIACETATE; WATER; REHMANNIA GLUTINOSA ROOT; HAEMATOCOCCUS PLUVIALIS; BUCKMINSTERFULLERENE; ISOHEXADECANE; POLYSORBATE 80; PHENOXYETHANOL; 1,2-HEXANEDIOL; HYDROXYACETOPHENONE; MEDIUM-CHAIN TRIGLYCERIDES; SORBITAN MONOOLEATE; SODIUM CHLORIDE; HYALURONATE SODIUM; HYDROLYZED WHEAT PROTEIN (ENZYMATIC, 3000 MW); PENTYLENE GLYCOL; PALMITOYL PENTAPEPTIDE-4; PALMITOYL TETRAPEPTIDE-7; BUTYLENE GLYCOL; ACETYL HEXAPEPTIDE-8; HEXAPEPTIDE-9; ROSA DAMASCENA FLOWER OIL; DIMETHICONE/VINYL DIMETHICONE CROSSPOLYMER (HARD PARTICLE); OAT BRAN; COLLAGEN, SOLUBLE, FISH SKIN; HYALURONIC ACID; PALMITOYL TRIPEPTIDE-5; POVIDONE; ETHYLHEXYLGLYCERIN; TITANIUM DIOXIDE; METHYLPARABEN; POLYSORBATE 20; PREZATIDE; MALTODEXTRIN; XANTHAN GUM; SORBITAN OLIVATE; ISONONYL ISONONANOATE; ALLANTOIN; EUGLENA GRACILIS; LACTOBACILLUS REUTERI F275 STRAIN; STANNIC OXIDE; CANOLA OIL; TERT-BUTYLHYDROQUINONE; UBIDECARENONE; ROSA RUGOSA FLOWER; ASTROCARYUM MURUMURU SEED BUTTER; DIMETHICONE

84601-003 Atti amour Rose Anti-Aging Repair Eye Cream

ACTIVE INGREDIENT

NIACINAMIDE 6.52%
GLYCERIN 2.24%

PURPOSE

Helps with skin whitening and wrinkle improvement

Keep out of reach of children mif swallowed , get medical help or contact a Poison Control center nght away

INDICATIONS AND USAGE

Helps with skin whitening and wrinkle improvement

When using this product mRefrain from using on wounds or damaged areas.Stop use and ask a doctorif many abnormal symptoms or side effects, such as redness.swvelling, or itching,occur in the area of applicatlon during or after using the cosmeticproduct.Keep out of reach of children if swallowed , get medical help or contact aPoison Control Center night away.

DOSAGE AND ADMINISTRATION

Take an appropriate amount of medication and apply it evenly to the desired area

INACTIVE INGREDIENT

SODIUM HYALURONATE
ROSA DAMASCENA FLOWER WATER
ROSA DAMASCENA FLOWER OIL
COFFEA ARABICA (COFFEE) SEED EXTRACT
ASTROCARYUM MURUMURU SEED BUTTER
DIMETHICONE
BUTYLENE GLYCOL
CETEARYL OLIVATE
SORBITAN OLIVATE
CETEARYL ALCOHOL
CYCLOPENTASILOXANE
ISONONYL ISONONANOATE
MICA
CI 77891
TIN OXIDE
WATER
REHMANNIA CHINENSIS ROOT EXTRACT
CANOLA OIL
TBHQ
OLIGOPEPTIDE-1
OLIGOPEPTIDE-5
OLIGOPEPTIDE-2
TOCOPHERYL ACETATE
METHYLPARABEN
PENTYLENE GLYCOL
AVENA SATIVA (OAT) BRAN EXTRACT
ALLANTOIN
EUGLENA GRACILIS POLYSACCHARIDE
UBIQUINONE
LACTOBACILLUS FERMENT
LACTOBACILLUS FERMENT LYSATE
ROSA RUGOSA FLOWER EXTRACT
HYDROXYACETOPHENONE
COLLAGEN
HYALURONIC ACID
HAEMATOCOCCUS PLUVIALIS EXTRACT
CAPRYLIC/CAPRIC TRIGLYCERIDE
SODIUM CHLORIDE
POLYSORBATE 20
TRIPEPTIDE-1
HEXAPEPTIDE-9
PALMITOYL TRIPEPTIDE-5
PALMITOYL PENTAPEPTIDE-4
PALMITOYL TETRAPEPTIDE-7
HYDROXYPROPYL TETRAHYDROPYRANTRIOL
DECAPEPTIDE-4
GLYCOPROTEINS
DISODIUM PHOSPHATE
DIPEPTIDE DIAMINOBUTYROYL BENZYLAMIDE DIACETATE
ACETYL HEXAPEPTIDE-8
DIMETHYL ISOSORBIDE
FULLERENES
PVP
ISOHEXADECANE
POLYSORBATE 80
SORBITAN OLEATE
PHENOXYETHANOL
ETHYLHEXYLGLYCERIN
MALTODEXTRIN
XANTHAN GUM
CYCLODEXTRIN

1,2-HEXANEDIOL